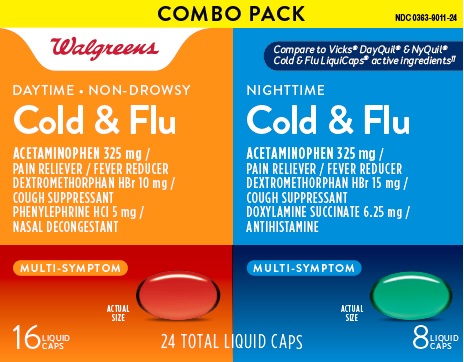 DRUG LABEL: Cold and Flu
NDC: 0363-9011 | Form: KIT | Route: ORAL
Manufacturer: Walgreens
Category: otc | Type: HUMAN OTC DRUG LABEL
Date: 20260119

ACTIVE INGREDIENTS: ACETAMINOPHEN 325 mg/1 1; DEXTROMETHORPHAN HYDROBROMIDE 10 mg/1 1; PHENYLEPHRINE HYDROCHLORIDE 5 mg/1 1; ACETAMINOPHEN 325 mg/1 1; DEXTROMETHORPHAN HYDROBROMIDE 15 mg/1 1; DOXYLAMINE SUCCINATE 6.25 mg/1 1
INACTIVE INGREDIENTS: FD&C YELLOW NO. 6; GELATIN; GLYCERIN; POLYETHYLENE GLYCOL 400; POVIDONE K30; PROPYLENE GLYCOL; SORBITOL; SORBITAN; WATER; TITANIUM DIOXIDE; FD&C RED NO. 40; D&C YELLOW NO. 10; FD&C BLUE NO. 1; GELATIN; GLYCERIN; POVIDONE K30; PROPYLENE GLYCOL; POLYETHYLENE GLYCOL 400; SORBITOL; SORBITAN; WATER; TITANIUM DIOXIDE

Walgreens Non-Drowsy Daytime & Nighttime Cold and Flu

Active ingredients (in each liquid-filled capsule) (Daytime Cold & Flu)

Acetaminophen 325 mg
Dextromethorphan HBr 10 mg
Phenylephrine HCl 5 mg

Purpose

Pain reliever/fever reducer
Cough suppressant
Nasal decongestant

Active ingredients (in each liquid-filled capsule) (Nighttime Cold & Flu)

Acetaminophen 325 mg
Dextromethorphan HBr 15 mg
Doxylamine succinate 6.25 mg

Purpose

Pain reliever/fever reducer
Cough suppressant
Antihistamine

Uses

- temporarily relieves common cold and flu symptoms:
  - fever
  - headache
  - sore throat
  - minor aches and pains
  - cough due to minor throat and bronchial irritation
  - nasal congestion (Daytime only)
  - runny nose and sneezing (Nighttime only)

Warnings

Liver warning: This product contains acetaminophen. Severe liver damage may occur if you take

- more than 4,000 mg of acetaminophen in 24 hours
- with other drugs containing acetaminophen
- 3 or more alcoholic drinks every day while using this product

Allergy alert: Acetaminophen may cause severe skin reactions. Symptoms may include:

- skin reddening
- blisters
- rash

If a skin reaction occurs, stop use and seek medical help right away.

Sore throat warning: If sore throat is severe, persists for more than 2 days, is accompanied or followed by fever, headache, rash, nausea, or vomiting, consult a doctor promptly.

Do not use

- with any other drug containing acetaminophen (prescription or nonprescription). If you are not sure whether a drug contains acetaminophen, ask a doctor or pharmacist.
- if you are now taking a prescription monoamine oxidase inhibitor (MAOI) (certain drugs for depression, psychiatric or emotional conditions, or Parkinson's disease), or for 2 weeks after stopping the MAOI drug. If you do not know if your prescription drug contains an MAOI, ask a doctor or pharmacist before taking this product.
- if you have ever had an allergic reaction to this product or any of its ingredients
- to make a child sleepy (Nighttime only)

Ask a doctor before use if you have

- cough that occurs with too much phlegm (mucus)
- liver disease
- difficulty in urination due to enlargement of the prostate gland
- heart disease (Daytime only)
- diabetes (Daytime only)
- thyroid disease (Daytime only)
- high blood pressure (Daytime only)
- persistent or chronic cough such as occurs with smoking, asthma, or emphysema (Daytime only)
- a breathing problem or chronic cough that lasts or as occurs with smoking, asthma, chronic bronchitis, or emphysema (Nighttime only)
- glaucoma (Nighttime only)

Ask a doctor or pharmacist before use if you are

- taking the blood thinning drug warfarin
- taking sedatives or tranquilizers (Nighttime only)

When using this product

- do not exceed recommended dosage
- excitability may occur, especially in children (Nighttime only)
- avoid alcoholic beverages (Nighttime only)
- marked drowsiness may occur (Nighttime only)
- alcohol, sedatives, and tranquilizers may increase drowsiness (Nighttime only)
- use caution when driving a motor vehicle or operating machinery (Nighttime only)

Stop use and ask a doctor if

- nervousness, dizziness, or sleeplessness occur (Daytime only)
- pain, nasal congestion, or cough gets worse or lasts more than 7 days (Daytime only)
- pain or cough gets worse or lasts more than 7 days (Nighttime only)
- fever gets worse or lasts more than 3 days
- redness or swelling is present
- new symptoms occur
- cough comes back or occurs with rash or headache that lasts. These could be signs of a serious condition.

If pregnant or breast-feeding,

ask a health professional before use.

Keep out of reach of children.

In case of accidental overdose, get medical help or contact a Poison Control Center (1-800-222-1222) right away. Prompt medical attention is critical for adults as well as for children even if you do not notice any signs or symptoms.

If taking NIGHTTIME and DAYTIME products, carefully read each section to ensure correct dosing.

Directions (Daytime only)

- do not take more than directed
- do not take more than 8 capsules per 24 hours
- adults and children 12 years and over: take 2 capsules with water every 4 hours
- children under 12 years: ask a doctor

Directions (Nighttime only)

- do not take more than directed
- do not take more than 8 capsules per 24 hours
- adults and children 12 years and over: take 2 capsules with water every 6 hours
- children under 12 years: ask a doctor

Other information

- TAMPER EVIDENT: DO NOT USE IF OUTER PACKAGE IS OPENED OR BLISTER IS TORN OR BROKEN
- store at 25ºC (77ºF); excursions permitted between 15º-30ºC (59º-86ºF)
- protect from heat, humidity and light
- see end flap for expiration date and lot number

Inactive ingredients (Daytime only)

FD&C Red# 40, FD&C Yellow# 6, gelatin, glycerin, polyethylene glycol,
povidone, propylene glycol, purified water, sorbitol sorbitan, titanium
dioxide

Inactive ingredients (Nighttime only)

D&C Yellow# 10, FD&C Blue# 1, gelatin, glycerin, polyethylene glycol,
povidone, propylene glycol, purified water, sorbitol sorbitan, titanium
dioxide

Questions or comments?

1-888-333-9792

PRINCIPAL DISPLAY PANEL

DAY & NIGHT PACK